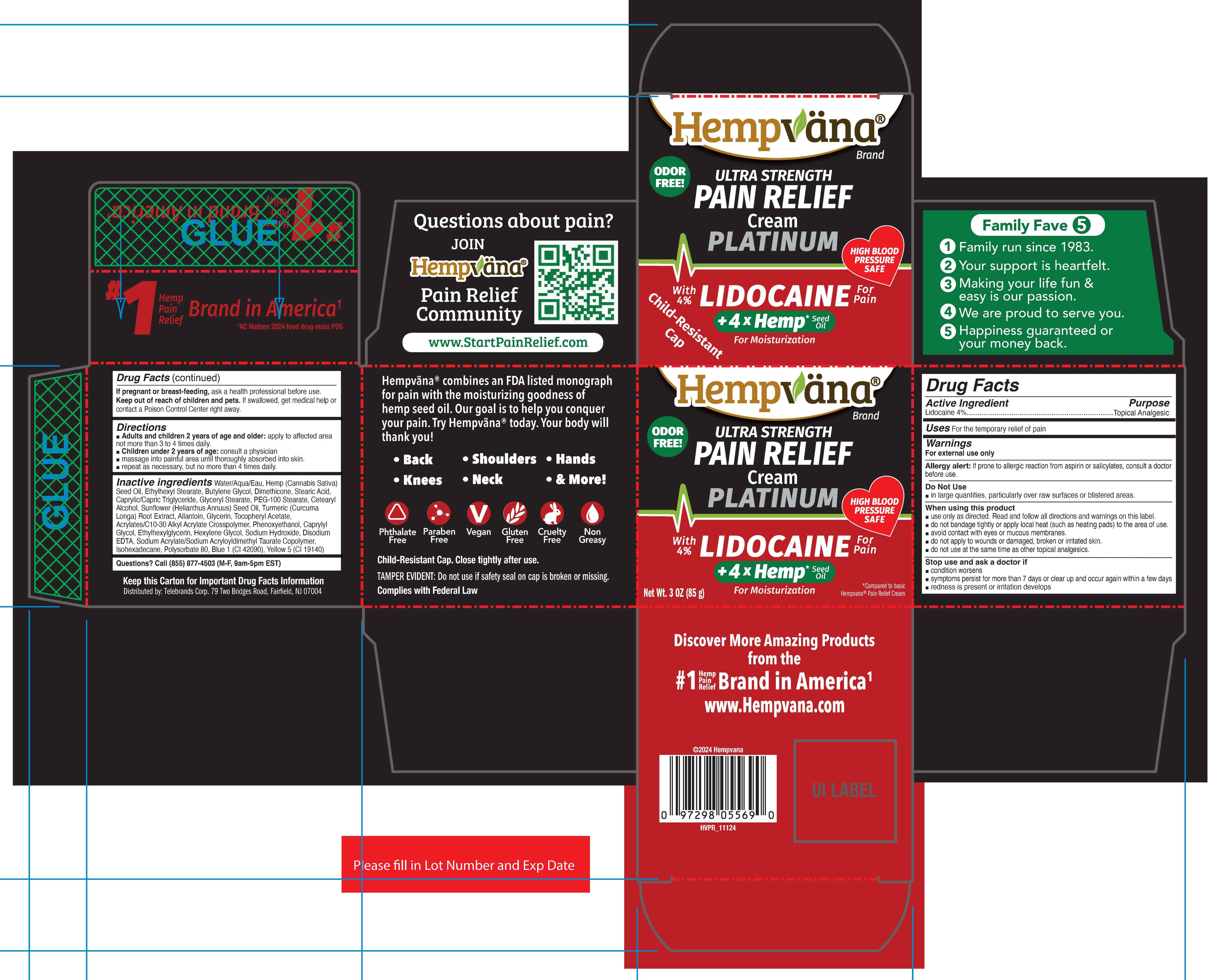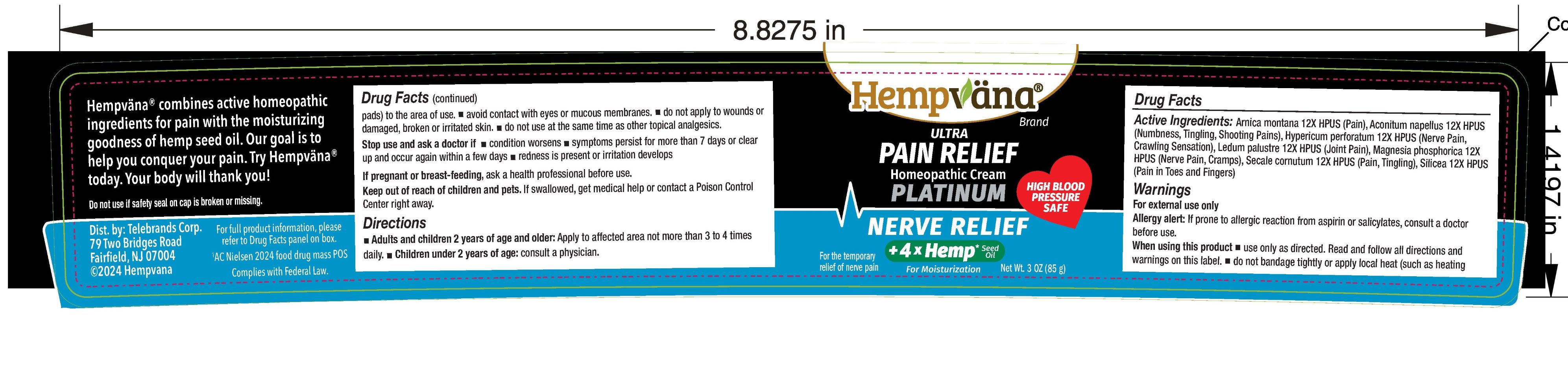 DRUG LABEL: Hempvana Ultra Strength Pain Relief Cream Platinum 4% Lidocaine
NDC: 73287-042 | Form: CREAM
Manufacturer: Telebrands Corp
Category: otc | Type: HUMAN OTC DRUG LABEL
Date: 20241121

ACTIVE INGREDIENTS: LIDOCAINE 4 g/100 g
INACTIVE INGREDIENTS: FD&C YELLOW NO. 5; FD&C BLUE NO. 1; GLYCERYL MONOSTEARATE; PEG-100 STEARATE; ALLANTOIN; .ALPHA.-TOCOPHEROL ACETATE; CARBOMER INTERPOLYMER TYPE A (ALLYL SUCROSE CROSSLINKED); PHENOXYETHANOL; ETHYLHEXYLGLYCERIN; ISOHEXADECANE; POLYSORBATE 80; BUTYLENE GLYCOL; WATER; ETHYLHEXYL STEARATE; DIMETHICONE; STEARIC ACID; MEDIUM-CHAIN TRIGLYCERIDES; CANNABIS SATIVA SEED OIL; CETOSTEARYL ALCOHOL; SUNFLOWER OIL; TURMERIC; GLYCERIN; CAPRYLYL GLYCOL; HEXYLENE GLYCOL; SODIUM HYDROXIDE; EDETATE DISODIUM ANHYDROUS; SODIUM ACRYLATE/SODIUM ACRYLOYLDIMETHYLTAURATE COPOLYMER (4000000 MW)

Hempvana Ultra Strength Pain Relief Cream Platinum 4% Lidocaine

Active Ingredient

Lidocaine 4%

Purpose

Lidocaine 4%..................Topical Analgesic

Uses

For the temporary relief of pain

Warnings

For external use only

Allergy alert:If prone to allergic reaction from aspirin or salicylates, consult a doctor before use.

Do Not Use

- in large quantities, particularly over raw surfaces or blistered areas

When using this product

- Use only as directed. Read and follow all directions and warnings on this label.
- Do not bandage tightly or apply local heat (such as heating pads) to the area of use.
- Avoid contact with eyes or mucous membranes.
- Do not apply to wounds or damaged, broken or irritated skin.
- Do not use at the same time as other topical analgesics.

Stop use and ask a doctor if

- Condition worsens
- Symptoms persist for more than 7 days or clear up and occur again within a few days
- Redness is present or irritation develops

PREGNANCY OR BREAST FEEDING

If pregnant or breast-feeding, ask a health professional before use.

Keep out of reach of children and pets. If swallowed, get medical help or contact a Poison Control Center right away.

Directions

- Adults and children 2 years of age and older:Apply to affected area not more than 3 to 4 times daily.
- Children under 2 years of age:consult a physician
- Apply generously to affected area.
- Massage into painful area until thoroughly absorbed into skin.
- Repeat as necessary, but no more than 4 times daily.

Inactive Ingredients

Water/Aqua/Eau, Ethylhexyl Stearate, Butylene Glycol, Dimethicone, Stearic Acid, Caprylic/Capric Triglyceride, Cannabis Sativa (Hemp) Seed Oil, Glyceryl Stearate, PEG-100 Stearate, Cetearyl Alcohol, Helianthus Annuus (Sunflower) Seed Oil, Curcuma Longa (Turmeric) Root Extract, Allantoin, Glycerin, Tocopheryl Acetate, Acrylates/C10-30 Alkyl Acrylate Crosspolymer, Phenoxyethanol, Caprylyl Glycol, Ethylhexylglycerin, Hexylene Glycol, Sodium Hydroxide, Disodium EDTA, Sodium Acrylate/Sodium Acryloyldimethyl Taurate Copolymer, Isohexadecane, Polysorbate 80, Blue 1 (CI 42090), Yellow 5 (CI 19140)

Questions?

Questions? Call (855) 877-4503 (M-F, 9am-5pm EST)

PACKAGE LABEL

Hempvana

Ultra Strength

Pain Relief

Cream

Platinum

with 4% Lidocaine

+4xHemp Seed Oil for moisturization

Net Wt. 3 OZ (85 g)